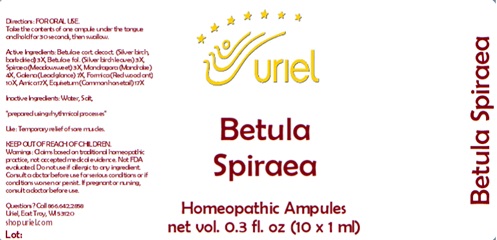 DRUG LABEL: Betula Spiraea
NDC: 48951-2068 | Form: LIQUID
Manufacturer: Uriel Pharmacy Inc.
Category: homeopathic | Type: HUMAN OTC DRUG LABEL
Date: 20240401

ACTIVE INGREDIENTS: BETULA PUBESCENS BARK 3 [hp_X]/1 mL; BETULA PUBESCENS LEAF 3 [hp_X]/1 mL; FILIPENDULA ULMARIA ROOT 3 [hp_X]/1 mL; MANDRAGORA OFFICINARUM ROOT 4 [hp_X]/1 mL; LEAD 7 [hp_X]/1 mL; FORMICA RUFA 10 [hp_X]/1 mL; ARNICA MONTANA 17 [hp_X]/1 mL; EQUISETUM ARVENSE TOP 17 [hp_X]/1 mL
INACTIVE INGREDIENTS: WATER; SODIUM CHLORIDE

Betula Spiraea

INDICATIONS AND USAGE

Directions: FOR ORAL USE.

DOSAGE AND ADMINISTRATION

Take the contents of one ampule
under the tongue and hold for
30 seconds, then swallow.

ACTIVE INGREDIENT

Active Ingredients: Betula e cort. decoct. (Silver birch, bark dried) 3X, Betula e fol. (Silver birch leaves) 3X, Spiraea (Meadowsweet) 3X, Mandragora (Mandrake) 4X, Galena (Lead glance) 7X, Formica (Red wood ant) 10X, Arnica 17X, Equisetum (Common horsetail) 17X

Inactive Ingredients: Water, Salt

PURPOSE

Use: Temporary relief of sore muscles.

KEEP OUT OF REACH OF CHILDREN.

WARNINGS

Warnings: Claims based on traditional homeopathic practice, not accepted medical evidence. Not FDA evaluated. Do not use if allergic to any ingredient. Consult a doctor before use for serious conditions or if conditions worsen or persist. If pregnant or nursing, consult a doctor before use.

Questions? Call 866.642.2858
Uriel, East Troy, WI 53120
shopuriel.com